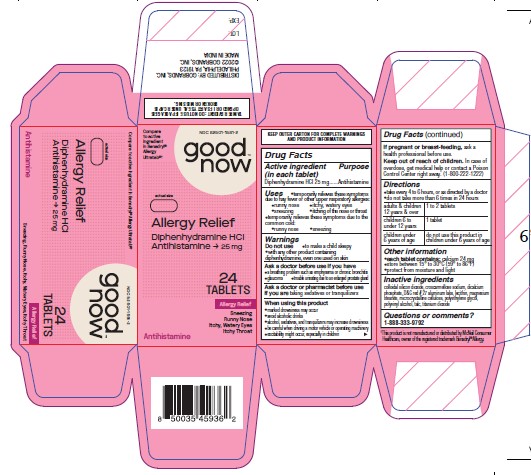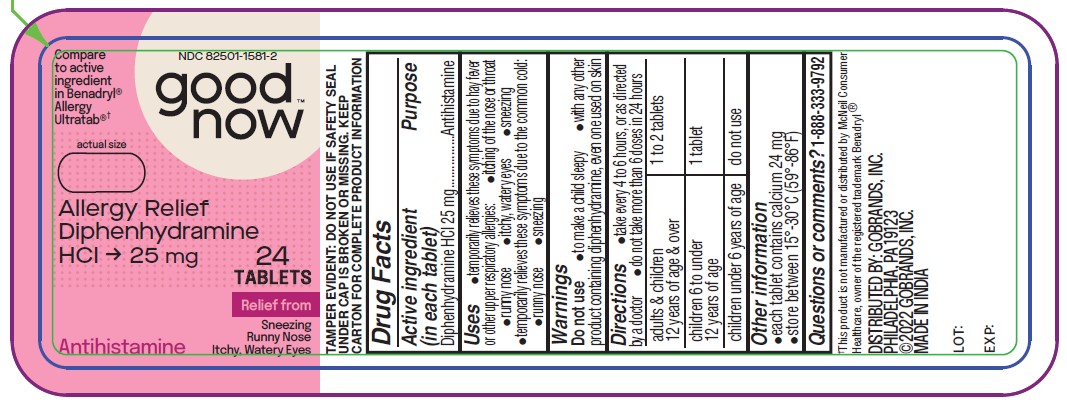 DRUG LABEL: Allergy Relief
NDC: 82501-1581 | Form: TABLET, FILM COATED
Manufacturer: Gobrands, Inc
Category: otc | Type: HUMAN OTC DRUG LABEL
Date: 20241220

ACTIVE INGREDIENTS: DIPHENHYDRAMINE HYDROCHLORIDE 25 mg/1 1
INACTIVE INGREDIENTS: SILICON DIOXIDE; CROSCARMELLOSE SODIUM; CALCIUM PHOSPHATE; D&C RED NO. 27; LECITHIN, SOYBEAN; MAGNESIUM STEARATE; MICROCRYSTALLINE CELLULOSE; POLYETHYLENE GLYCOL, UNSPECIFIED; POLYVINYL ALCOHOL, UNSPECIFIED; TALC; TITANIUM DIOXIDE

Allergy Relief

Active ingredient (in each tablet)

Diphenhydramine HCl 25 mg

Purpose

Antihistamine

Uses

• temporarily relieves these symptoms due to hay fever or other upper respiratory allergies:
• runny nose
• itchy, watery eyes
• sneezing
• itching of the nose or throat
• temporarily relieves these symptoms due to the common cold:
• runny nose
• sneezing

Warnings

Do not use • for children under 12 years of age • with any other product containing diphenhydramine, even one used on skin.

Ask a doctor before use if you have
• a breathing problem such as emphysema or chronic bronchitis • glaucoma
• difficulty in urination due to enlargement of the prostate gland

Ask a doctor or pharmacist before use if you are taking sedatives or tranquilizers

When using this product • avoid alcoholic beverages

Stop use and ask a doctor if sleeplessness persists continuously for more than 2 weeks. Insomnia may be a symptom of serious underlying medical illness.

PREGNANCY OR BREAST FEEDING

If pregnant or breast-feeding, ask a health professional before use.

Keep out of reach of children. In case of overdose, get medical help or contact a Poison Control Center right away. (1-800-222-1222)

Directions

• take only one dose per day (24 hours)

adults & children 12 years & over | take 2 softgels at bedtime if needed or as directed by a doctor
children under 12 years | do not use

Other information

• store at 20-25° C (68-77° F) • avoid excessive heat above 40° C (104° F) and high humidity • Protect from light

Inactive ingredients

colloidal silicon dioxide, croscarmellose sodium, dicalcium phosphate, D&C red # 27 aluminum lake, lecithin, magnesium stearate, microcrystalline cellulose, polyethylene glycol, polyvinyl alcohol, talc, titanium dioxide

Questions or comments?

1-888-333-9792